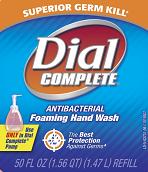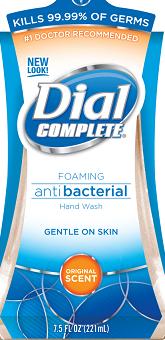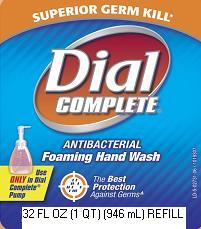 DRUG LABEL: Dial Complete Antibacterial Foaming Hand Wash with Lotion
NDC: 54340-778 | Form: SOLUTION
Manufacturer: The Dial Corporation
Category: otc | Type: HUMAN OTC DRUG LABEL
Date: 20100122

ACTIVE INGREDIENTS: TRICLOSAN 0.46 mL/1000 mL

Drug Facts

Active Ingredient - TRICLOSAN 0.46%

Purpose - Antibacterial

PURPOSE

Uses - For handwashing to decrease bacteria on the skin

Warnings - For external use only

When using this product avoid contact with eyes. In case of eye contact, flush with water.

Stop use and ask a doctor if irritation and redness develops.

Keep out of reach of children. If swallowed, get medical help or contact a Poison Control Center right away.

Directions: Pump into DRY hands. Lather vigorously for at lest 15 seconds. Rinse and dry thoroughly.

INACTIVE INGREDIENT

Inactive Ingredients:Water, Sodium Xylenesulfonate, Dipropylene Glycol, Glycerin, Sodium PCA, Ammonium Lauryl Sulfate, Cocamidopropyl Betaine, Polyquaternium-10, Fragrance, Disodium Phosphate, Cetyl Alcohol, Aloe-Barbadensis Leaf Juice, Citric Acid, Methylparaben, Propylparaben, Red 4, Yellow 5

Questions? 1-800-258-DIAL (3425)